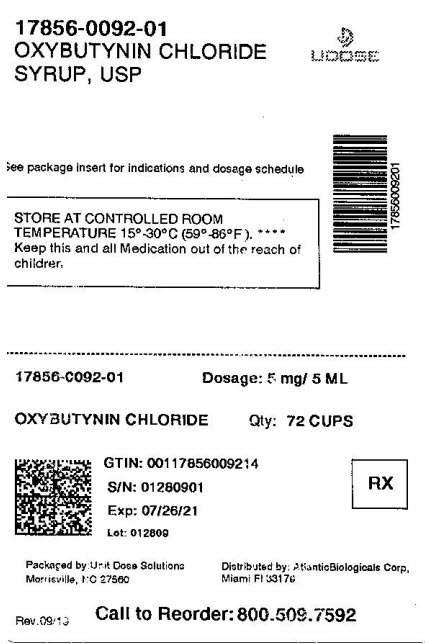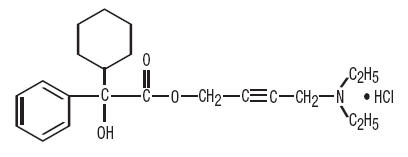 DRUG LABEL: Oxybutynin Chloride
NDC: 17856-0092 | Form: SYRUP
Manufacturer: Atlantic Biologicals Corps
Category: prescription | Type: HUMAN PRESCRIPTION DRUG LABEL
Date: 20210127

ACTIVE INGREDIENTS: OXYBUTYNIN CHLORIDE 5 mg/5 mL
INACTIVE INGREDIENTS: Water; Trisodium Citrate Dihydrate; Anhydrous Citric Acid; Sucrose; Sorbitol; Glycerin; Propylene Glycol; Methylparaben; FD&C Blue No. 1; D&C Yellow No. 10

OXYBUTYNIN CHLORIDE
SYRUP, USP
5 mg/5 mL

DESCRIPTION

Chemically, oxybutynin chloride is 4-(Diethylamino)-2-butynyl (±)-α-phenylcyclohexaneglycolate hydrochloride. The molecular formula of oxybutynin chloride is C22H31NO3•HCl. The structural formula appears below:

Oxybutynin chloride is a white crystalline solid with a molecular weight of 393.96. It is readily soluble in water and acids, but relatively insoluble in alkalis.

Each 5 mL, for oral administration, contains 5 mg of oxybutynin chloride. In addition, the following inactive ingredients are present: Artificial raspberry flavor; citric acid, USP; D&C Yellow No. 10; FD&C Blue No. 1; glycerin, USP; liquid sugar; methylparaben, NF; propylene glycol, USP; sodium citrate, USP and sorbitol solution, USP.

Therapeutic Category: Antispasmodic, anticholinergic.

CLINICAL PHARMACOLOGY

Oxybutynin chloride exerts direct antispasmodic effect on smooth muscle and inhibits the muscarinic action of acetylcholine on smooth muscle. Oxybutynin chloride exhibits only one fifth of the anticholinergic activity of atropine on the rabbit detrusor muscle, but four to ten times the antispasmodic activity. No blocking effects occur at skeletal neuromuscular junctions or autonomic ganglia (antinicotinic effects).

Oxybutynin chloride relaxes bladder smooth muscle. In patients with conditions characterized by involuntary bladder contractions, cystometric studies have demonstrated that oxybutynin chloride increases bladder (vesical) capacity, diminishes the frequency of uninhibited contractions of the detrusor muscle, and delays the initial desire to void. Oxybutynin chloride thus decreases urgency and the frequency of both incontinent episodes and voluntary urination.

Oxybutynin chloride was well tolerated in patients administered the drug in controlled studies of 30 days duration and in uncontrolled studies in which some patients received the drug for 2 years. Pharmacokinetic information is not currently available.

INDICATIONS AND USAGE

Oxybutynin chloride syrup is indicated for the relief of symptoms of bladder instability associated with voiding in patients with uninhibited neurogenic or reflex neurogenic bladder (ie, urgency, frequency, urinary leakage, urge incontinence, dysuria).

CONTRAINDICATIONS

Oxybutynin chloride is contraindicated in patients with untreated angle closure glaucoma and in patients with untreated narrow anterior chamber angles since anticholinergic drugs may aggravate these conditions.

It is also contraindicated in partial or complete obstruction of the gastrointestinal tract, paralytic ileus, intestinal atony of the elderly or debilitated patient, megacolon, toxic megacolon complicating ulcerative colitis, severe colitis, and myasthenia gravis. It is contraindicated in patients with obstructive uropathy and in patients with unstable cardiovascular status in acute hemorrhage.

Oxybutynin chloride is contraindicated in patients who have demonstrated hypersensitivity to the product.

WARNINGS

Oxybutynin chloride, when administered in the presence of a high environmental temperature, can cause heat prostration (fever and heat stroke due to decreased sweating). Diarrhea may be an early symptom of incomplete intestinal obstruction, especially in patients with ileostomy, or colostomy. In this instance treatment with oxybutynin chloride would be inappropriate and possibly harmful.

Oxybutynin chloride may produce drowsiness or blurred vision. The patient should be cautioned regarding activities requiring mental alertness such as operating a motor vehicle or other machinery or performing hazardous work while taking this drug.

Alcohol or other sedative drugs may enhance the drowsiness caused by oxybutynin chloride.

PRECAUTIONS

Oxybutynin chloride should be used with caution in the elderly and in all patients with autonomic neuropathy, hepatic or renal disease. Oxybutynin chloride may aggravate the symptoms of hyperthyroidism, coronary heart disease, congestive heart failure, cardiac arrhythmias, hiatal hernia, tachycardia, hypertension, and prostatic hypertrophy.

Administration of oxybutynin chloride to patients with ulcerative colitis may suppress intestinal motility to the point of producing a paralytic ileus and precipitate or aggravate toxic megacolon, a serious complication of the disease.

Carcinogenesis, Mutagenesis, Impairment of Fertility

A 24-month study in rats at dosages up to approximately 400 times the recommended human dosage showed no evidence of carcinogenicity.

Oxybutynin chloride showed no increase of mutagenic activity when tested in Schizosaccharomyces pompholiciformis, Saccharomyces cerevisiae and Salmonella typhimurium test systems. Reproduction studies in the hamster, rabbit, rat, and mouse have shown no definite evidence of impaired fertility.

Pregnancy

Teratogenic Effects-Pregnancy Category B

Reproduction studies in the hamster, rabbit, rat, and mouse have shown no definite evidence of impaired fertility or harm to the animal fetus. The safety of oxybutynin chloride administered to women who are or who may become pregnant has not been established. Therefore, oxybutynin chloride should not be given to pregnant women unless, in the judgment of the physician, the probable clinical benefits outweigh the possible hazards.

Nursing Mothers

It is not known whether this drug is excreted in human milk. Because many drugs are excreted in human milk, caution should be exercised when oxybutynin chloride is administered to a nursing woman.

Pediatric Use

The safety and efficacy of oxybutynin chloride administration have been demonstrated for pediatric patients 5 years of age and older (see DOSAGE AND ADMINISTRATION). However, as there is insufficient clinical data for pediatric patients under age 5, oxybutynin chloride is not recommended for this age group.

ADVERSE REACTIONS

Following administration of oxybutynin chloride, the symptoms that can be associated with the use of other anticholinergic drugs may occur:

Cardiovascular: Palpitations, tachycardia, vasodilatation

Dermatologic: Decreased sweating, rash

Gastrointestinal/Genitourinary: Constipation, decreased gastrointestinal motility, dry mouth, nausea, urinary hesitance and retention

Nervous System: Asthenia, dizziness, drowsiness, hallucinations, insomnia, restlessness

Ophthalmic: Amblyopia, cycloplegia, decreased lacrimation, mydriasis

Other: Impotence, suppression of lactation

OVERDOSAGE

The symptoms of overdosage with oxybutynin chloride may be any of those seen with other anticholinergic agents. Symptoms may include signs of central nervous system excitation (eg, restlessness, tremor, irritability, convulsions, delirium, hallucinations), flushing, fever, nausea, vomiting, tachycardia, hypotension or hypertension, respiratory failure, paralysis, and coma. In the event of an overdose or exaggerated response, treatment should be symptomatic and supportive. Maintain respiration and induce emesis or perform gastric lavage (emesis is contraindicated in precomatose patients, convulsive or psychotic state). Activated charcoal may be administered as well as a cathartic. Physostigmine may be considered to reverse symptoms of anticholinergic intoxication. Hyperpyrexia may be treated symptomatically with ice bags or other cold applications and sponges.

DOSAGE AND ADMINISTRATION

Adults

The usual dose is one teaspoonful (5 mg/5 mL) syrup two to three times a day. The maximum recommended dose is one teaspoonful (5 mg/5 mL) syrup four times a day.

Children over 5 years of age

The usual dose is one teaspoonful (5 mg/5 mL) two times a day. The maximum recommended dose is one teaspoonful (5 mg/5 mL) three times a day.

HOW SUPPLIED

Product: 17856-0092

NDC: 17856-0092-1 5 mL in a CUP

Rx Only

Product No.: 8092

Manufactured By:
Morton Grove Pharmaceuticals, Inc.
Morton Grove, IL 60053

A50-8092-16
REV. 11-04